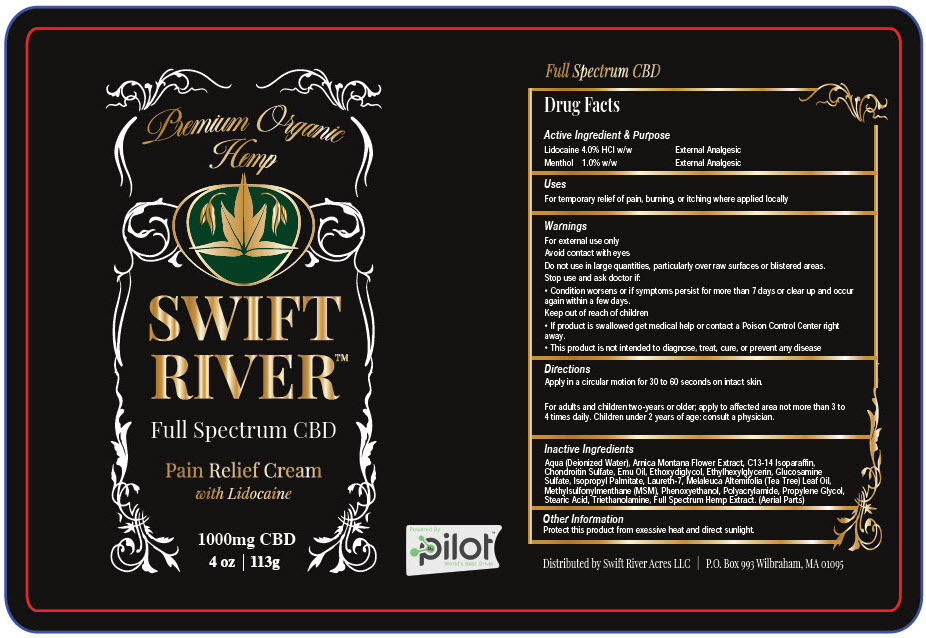 DRUG LABEL: Swift River Pain Relief
NDC: 73596-200 | Form: CREAM
Manufacturer: Philia Group LLC
Category: otc | Type: HUMAN OTC DRUG LABEL
Date: 20200813

ACTIVE INGREDIENTS: Lidocaine Hydrochloride 4000 mg/113 g; MENTHOL, UNSPECIFIED FORM 1000 mg/113 g
INACTIVE INGREDIENTS: WATER; ARNICA MONTANA FLOWER; C13-14 ISOPARAFFIN; EMU OIL; DIETHYLENE GLYCOL MONOETHYL ETHER; ETHYLHEXYLGLYCERIN; GLUCOSAMINE SULFATE; ISOPROPYL PALMITATE; LAURETH-7; TEA TREE OIL; DIMETHYL SULFONE; PHENOXYETHANOL; PROPYLENE GLYCOL; STEARIC ACID; TROLAMINE

Swift River™ Pain Relief

Drug Facts

ACTIVE INGREDIENT

Active Ingredient & Purpose
Lidocaine 4.0% HCl w/w | External Analgesic
Menthol 1.0% w/w | External Analgesic

Uses

For temporary relief of pain, burning, or itching where applied locally

Warnings

For external use only

Avoid contact with eyes

Do not use in large quantities, particularly over raw surfaces or blistered areas.

Stop use and ask doctor if

- Condition worsens or if symptoms persist for more than 7 days or clear up and occur again within a few days.

Keep out of reach of children

- If product is swallowed get medical help or contact a Poison Control Center right away.
- This product is not intended to diagnose, treat, cure, or prevent any disease

Directions

Apply in a circular motion for 30 to 60 seconds on intact skin.

For adults and children two-years or older; apply to affected area not more than 3 to 4 times daily. Children under 2 years of age: consult a physician.

Inactive Ingredients

Aqua (Deionized Water), Arnica Montana Flower Extract, C13-14 Isoparaffin, Chondroitin Sulfate, Emu Oil, Ethoxydiglycol, Ethylhexylglycerin, Glucosamine Sulfate, Isopropyl Palmitate, Laureth-7, Melaleuca Altemifolia (Tea Tree) Leaf Oil, Methylsulfonylmenthane (MSM), Phenoxyethanol, Polyacrylamide, Propylene Glycol, Stearic Acid, Triethanolamine, Full Spectrum Hemp Extract. (Aerial Parts)

Other Information

Protect this product from exessive heat and direct sunlight.

Distributed by Swift River Acres LLC | P.O. Box 993 Wilbraham, MA 01095

PRINCIPAL DISPLAY PANEL - 113 g Bottle Label

Premium Organic
Hemp

SWIFT
RIVER™

Full Spectrum CBD

Pain Relief Cream
with Lidocaine

1000mg CBD

4 oz | 113g

Powered By
pilot™
World's Best Driver